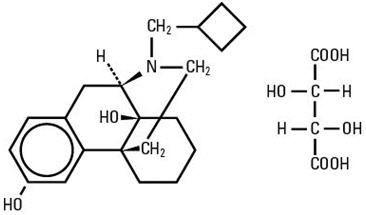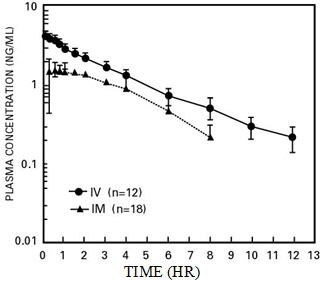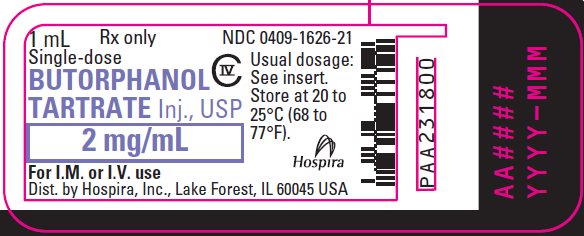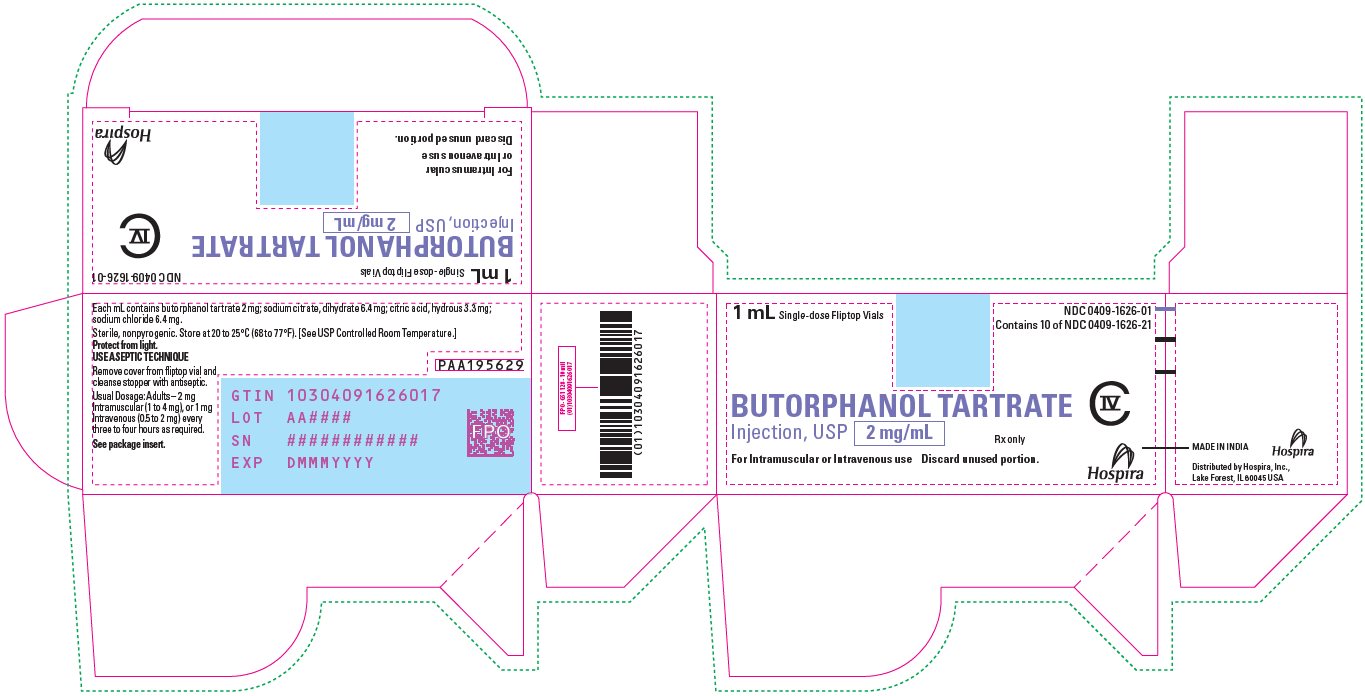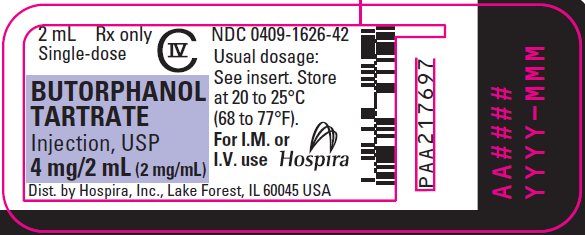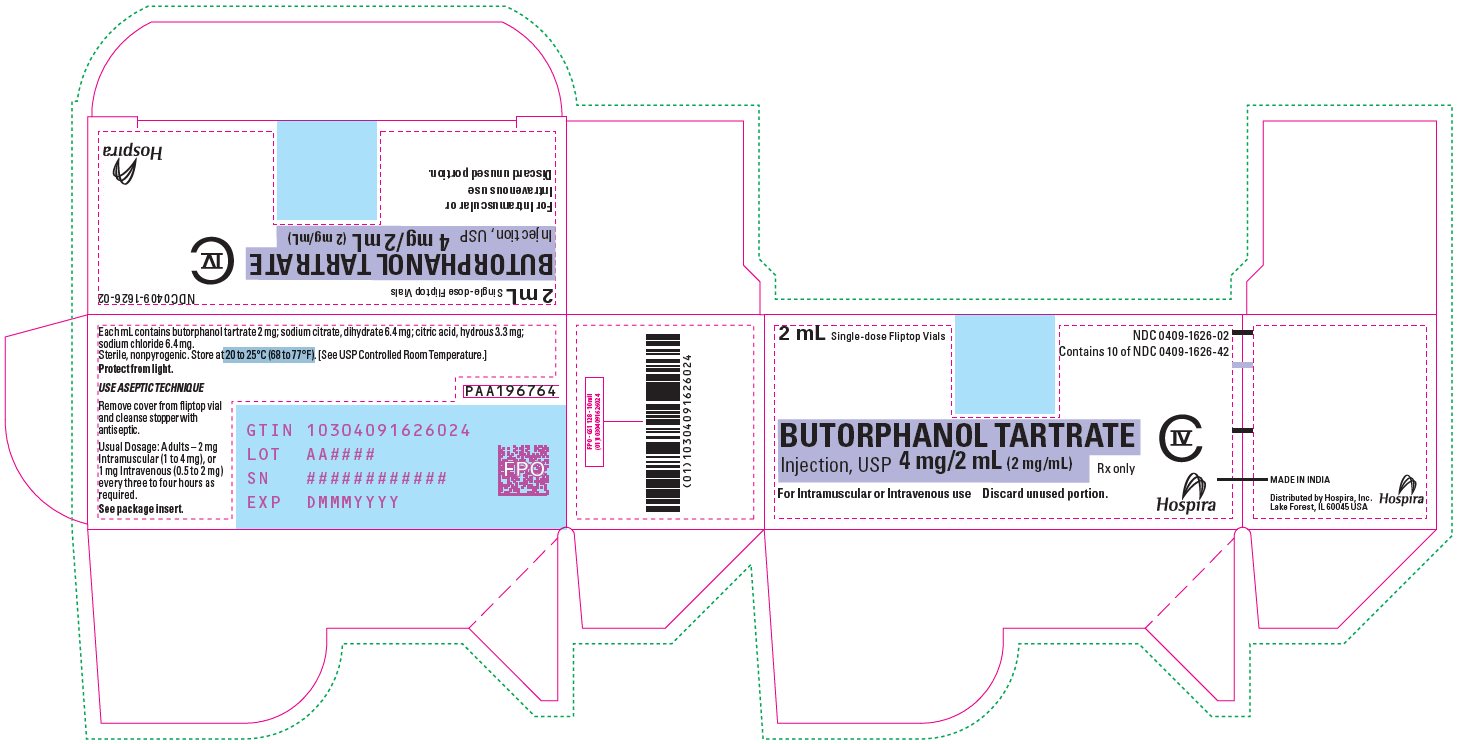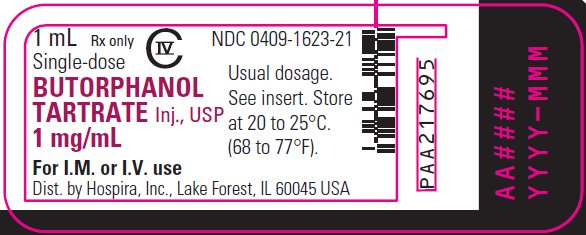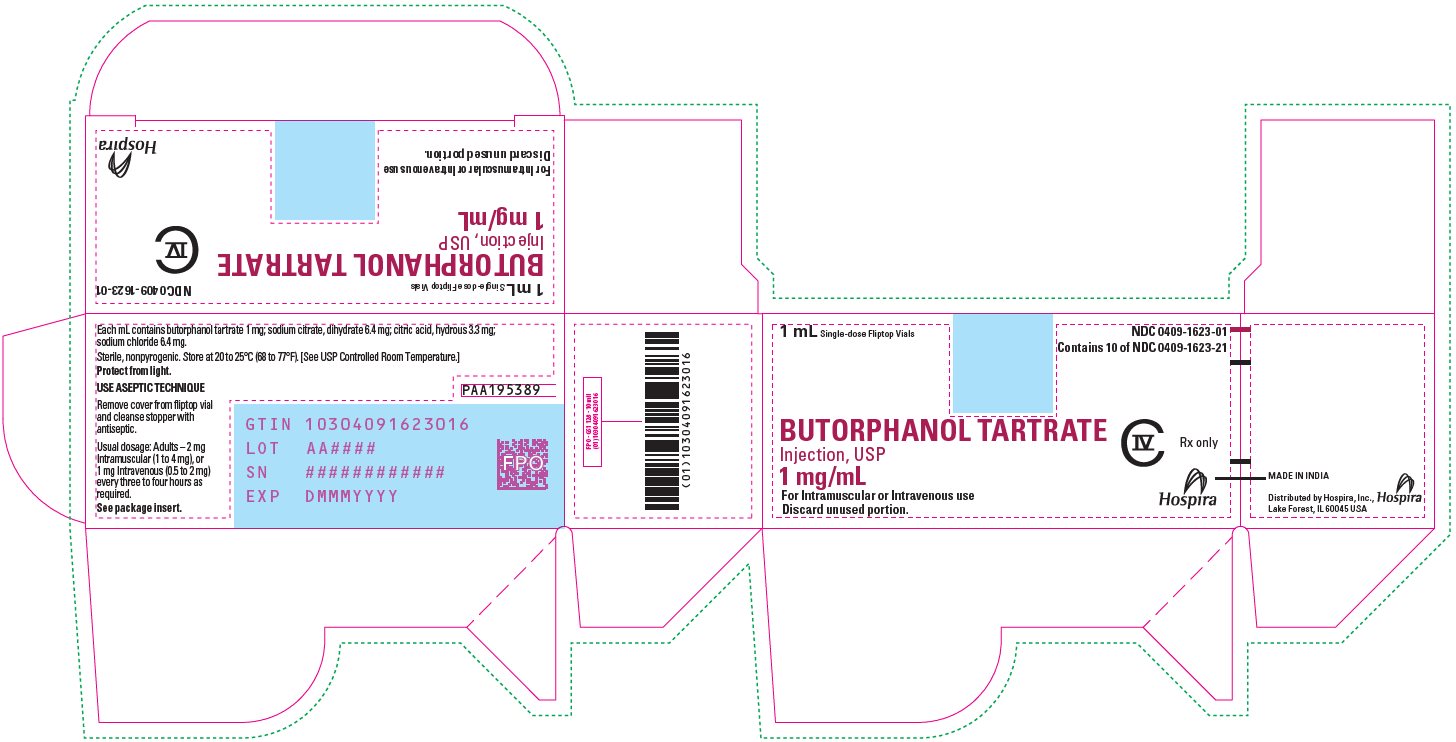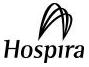 DRUG LABEL: Butorphanol Tartrate
NDC: 0409-1626 | Form: INJECTION, SOLUTION
Manufacturer: Hospira, Inc.
Category: prescription | Type: HUMAN PRESCRIPTION DRUG LABEL
Date: 20260102
DEA Schedule: CIV

ACTIVE INGREDIENTS: BUTORPHANOL TARTRATE 2 mg/1 mL
INACTIVE INGREDIENTS: TRISODIUM CITRATE DIHYDRATE 6.4 mg/1 mL; CITRIC ACID MONOHYDRATE 3.3 mg/1 mL; SODIUM CHLORIDE 6.4 mg/1 mL; WATER

Butorphanol Tartrate Injection, USP CIV

WARNING: SERIOUS AND LIFE-THREATENING RISKS FROM USE OF BUTORPHANOL TARTRATE INJECTION

Addiction, Abuse, and Misuse

Because the use of Butorphanol Tartrate Injection exposes patients and other users to the risks of opioid addiction, abuse, and misuse, which can lead to overdose and death, assess each patient’s risk prior to prescribing and reassess all patients regularly for the development of these behaviors and conditions [see WARNINGS].

Life-Threatening Respiratory Depression

Serious, life-threatening, or fatal respiratory depression may occur with use of Butorphanol Tartrate Injection, especially during initiation or following a dosage increase. To reduce the risk of respiratory depression, proper dosing and titration ‎of Butorphanol Tartrate Injection are essential [see WARNINGS].

Risks From Concomitant Use With Benzodiazepines Or Other CNS Depressants

Concomitant use of opioids with benzodiazepines or other central nervous system (CNS) depressants, including alcohol, may result in profound sedation, respiratory depression, coma, and death. Reserve concomitant prescribing of Butorphanol Tartrate Injection and benzodiazepines or other CNS depressants for use in patients for whom alternative treatment options are inadequate [see WARNINGS, PRECAUTIONS; Drug Interactions].

Neonatal Opioid Withdrawal Syndrome (NOWS)

Advise pregnant women using opioids for an extended period of time of the risk of Neonatal Opioid Withdrawal Syndrome, which may be life-threatening if not recognized and treated. Ensure that management by neonatology experts‎ will be available at delivery [see WARNINGS].

DESCRIPTION

Butorphanol tartrate is a synthetically derived opioid agonist-antagonist analgesic of the phenanthrene series. The chemical name is (-)-17-(cyclobutylmethyl) morphinan-3, 14-diol D-(-)- tartrate (1:1) (salt). The molecular formula is C21H29NO2 ∙ C4H6O6, which corresponds to a molecular weight of 477.56 and the following structural formula:

Butorphanol tartrate is a white crystalline substance. The dose is expressed as the tartrate salt. One milligram of the salt is equivalent to 0.68 mg of the free base. The n-octanol/aqueous buffer partition coefficient of butorphanol is 180:1 at pH 7.5.

Butorphanol Tartrate Injection is a sterile, nonpyrogenic parenteral aqueous solution of butorphanol tartrate for intravenous or intramuscular administration.

Each milliliter (mL) contains butorphanol tartrate 1 or 2 mg; sodium citrate, dihydrate, 6.4 mg; citric acid hydrous 3.3 mg; sodium chloride 6.4 mg. The pH is 4.5 (3.0 to 5.5).

CLINICAL PHARMACOLOGY

Mechanism of Action

Butorphanol is a partial opioid agonist at the mu opioid receptor and a full agonist at the kappa opioid receptor. The principal therapeutic action of butorphanol is analgesia. Clinically, dosage is titrated to provide adequate analgesia and may be limited by adverse reactions, including respiratory and CNS depression.

The precise mechanism of the analgesic action is unknown. However, specific CNS opioid receptors for endogenous compounds with opioid-like activity have been identified throughout the brain and spinal cord and are thought to play a role in the analgesic effects of this drug.

Pharmacodynamics

The analgesic effect of butorphanol is influenced by the route of administration. Onset of analgesia is within a few minutes for intravenous administration and within 15 minutes for intramuscular injection.

Peak analgesic activity occurs within 30 to 60 minutes following intravenous and intramuscular administration.

The duration of analgesia varies depending on the pain model as well as the route of administration, but is generally 3 to 4 hours with IM and IV doses as defined by the time 50% of patients required remedication. In postoperative studies, the duration of analgesia with IV or IM butorphanol was similar to morphine, meperidine and pentazocine when administered in the same fashion at equipotent doses [see Clinical Trials].

Effects on the Central Nervous System

Butorphanol produces respiratory depression by direct action on brain stem respiratory centers. The respiratory depression involves a reduction in the responsiveness of the brain stem respiratory centers to both increases in carbon dioxide tension and electrical stimulation.

In human studies involving individuals without significant respiratory dysfunction, 2 mg of butorphanol IV and 10 mg of morphine sulfate IV depressed respiration to a comparable degree. At higher doses, the magnitude of respiratory depression with butorphanol is not appreciably increased; however, the duration of respiratory depression is longer. Respiratory depression noted after administration of butorphanol to humans by any route is reversed by treatment with naloxone, a specific opioid antagonist [see OVERDOSAGE].

Butorphanol, like other mixed agonist-antagonists with a high affinity for the kappa receptor, may produce unpleasant psychotomimetic effects in some individuals.

Nausea and/or vomiting may be produced by doses of 1 mg or more administered by any route.

In human studies of butorphanol [see CLINICAL PHARMACOLOGY; Clinical Trials], sedation is commonly noted at doses of 0.5 mg or more. Narcosis is produced by 10 to 12 mg doses of butorphanol administered over 10 to 15 minutes intravenously.

Butorphanol causes miosis, even in total darkness. Pinpoint pupils are a sign of opioid overdose but are not pathognomonic (e.g., pontine lesions of hemorrhagic or ischemic origins may produce similar findings). Marked mydriasis rather than miosis may be seen due to hypoxia in overdose situations.

Effects on the Gastrointestinal Tract and Other Smooth Muscle

Butorphanol causes a reduction in motility associated with an increase in smooth muscle tone in the antrum of the stomach and duodenum. Digestion of food in the small intestine is delayed and propulsive contractions are decreased. Propulsive peristaltic waves in the colon are decreased, while tone may be increased to the point of spasm, resulting in constipation. Other opioid-induced effects may include a reduction in biliary and pancreatic secretions, spasm of sphincter of Oddi, transient elevations in serum amylase, and opioid-induced esophageal dysfunction (OIED).

Effects on the Cardiovascular System

Hemodynamic changes noted during cardiac catheterization in patients receiving single 0.025 mg/kg intravenous doses of butorphanol have included increases in pulmonary artery pressure, wedge pressure and vascular resistance, increases in left ventricular end diastolic pressure and in systemic arterial pressure.

Effects on the Endocrine System

Opioids inhibit the secretion of adrenocorticotropic hormone (ACTH), cortisol, and luteinizing hormone (LH) in humans [see ADVERSE REACTIONS]. They also stimulate prolactin, growth hormone (GH) secretion, and pancreatic secretion of insulin and glucagon.

Use of opioids for an extended period of time may influence the hypothalamic-pituitary-gonadal axis, leading to androgen deficiency that may manifest as low libido, impotence, erectile dysfunction, amenorrhea, or infertility. The causal role of opioids in the clinical syndrome of hypogonadism is unknown because the various medical, physical, lifestyle, and psychological stressors that may influence gonadal hormone levels have not been adequately controlled for in studies conducted to date [see ADVERSE REACTIONS].

Effects on the Immune System

Opioids have been shown to have a variety of effects on components of the immune system. The clinical significance of these findings is unknown. Overall, the effects of opioids appear to be modestly immunosuppressive.

Concentration–Efficacy Relationships

The minimum effective analgesic concentration will vary widely among patients, especially among patients who have been previously treated with opioid agonists. The minimum effective analgesic concentration of butorphanol for any individual patient may increase over time due to an increase in pain, the development of a new pain syndrome, and/or the development of analgesic tolerance [see DOSAGE AND ADMINISTRATION].

Concentration–Adverse Reaction Relationships

There is a relationship between increasing butorphanol plasma concentration and increasing frequency of dose-related opioid adverse reactions such as nausea, vomiting, CNS effects, and respiratory depression. In opioid-tolerant patients, the situation may be altered by the development of tolerance to opioid-related adverse reactions [see DOSAGE AND ADMINISTRATION].

Pharmacokinetics

Butorphanol Tartrate Injection is rapidly absorbed after IM injection and peak plasma levels are reached in 20 to 40 minutes.

Following its initial absorption/distribution phase, the single-dose pharmacokinetics of butorphanol by the intravenous and intramuscular routes of administration are similar (see Figure 1).

Figure 1—Butorphanol Plasma Levels After IV and IM Administration of 2 mg Dose

Serum protein binding is independent of concentration over the range achieved in clinical practice (up to 7 ng/mL) with a bound fraction of approximately 80%.

The volume of distribution of butorphanol varies from 305 to 901 liters and total body clearance from 52 to 154 liters/hr (see Table 1).

Table 1—Mean Pharmacokinetic Parameters of Intravenous Butorphanol in Young and Elderly Subjects [Young subjects (n=24) are from 20 to 40 years old and elderly (n=24) are greater than 65 years of age.]
Parameters | Young | Elderly
AUC (inf) [Area under plasma concentration-time curve after a 1 mg dose.] | 7.24 (1.57) [Mean (1S.D.).] | 8.71 (2.02)
(hr ∙ ng/mL) | (4.40–9.77) [(range of observed values).] | (4.76–13.03)
Half-life (hr) | 4.56 (1.67) | 5.61 (1.36)
 | (2.06–8.70) | (3.25–8.79)
Volume of Distribution [Derived from IV data.] (L) | 487 (155) (305–901) | 552 (124) (305–737)
Total body | 99 (23) | 82 (21)
Clearance (L/hr) | (70–154) | (52–143)

The drug is transported across the blood-brain and placental barriers and into human milk [see PRECAUTIONS: Labor or Delivery and Nursing Mothers].

Butorphanol is extensively metabolized in the liver. Metabolism is qualitatively and quantitatively similar following intravenous or intramuscular administration. Oral bioavailability is only 5 to 17% because of extensive first pass metabolism of butorphanol.

The major metabolite of butorphanol is hydroxybutorphanol, while norbutorphanol is produced in small amounts. Both have been detected in plasma following administration of butorphanol, with norbutorphanol present at trace levels at most time points. The elimination half-life of hydroxybutorphanol is about 18 hours and, as a consequence, considerable accumulation (~5-fold) occurs when butorphanol is dosed to steady state.

Elimination occurs by urine and fecal excretion. When ^3H labeled butorphanol is administered to normal subjects, most (70 to 80%) of the dose is recovered in the urine, while approximately 15% is recovered in the feces.

About 5% of the dose is recovered in the urine as butorphanol. Forty-nine percent is eliminated in the urine as hydroxybutorphanol. Less than 5% is excreted in the urine as norbutorphanol.

Butorphanol pharmacokinetics in the elderly differ from younger patients (see Table 1).

In renally impaired patients with creatinine clearances <30 mL/min, the elimination half-life was approximately doubled and the total body clearance was approximately one half (10.5 hours [clearance 150 L/h] compared to 5.8 hours [clearance 260 L/h] in healthy subjects). No effect on Cmax or Tmax was observed after a single-dose.

After intravenous administration to patients with hepatic impairment, the elimination half-life of butorphanol was approximately tripled and total body clearance was approximately one half (half-life 16.8 hours, clearance 92 L/h) compared to healthy subjects (half-life 4.8 hours, clearance 175 L/h). The exposure of hepatically impaired patients to butorphanol was significantly greater (about 2-fold) than that in healthy subjects [see PRECAUTIONS: Hepatic and Renal Disease, Drug Interactions and Geriatric Use and CLINICAL PHARMACOLOGY: Individualization of Dosage].

Clinical Trials

The effectiveness of opioid analgesics varies in different pain syndromes. Studies with Butorphanol Tartrate Injection have been performed in postoperative (primarily abdominal and orthopedic) pain and pain during labor and delivery, as preoperative and preanesthetic medication, and as a supplement to balanced anesthesia (see below).

Use in the Management of Pain-Postoperative Pain

The analgesic efficacy of Butorphanol Tartrate Injection in postoperative pain was investigated in several double-blind active-controlled studies involving 958 butorphanol-treated patients. The following doses were found to have approximately equivalent analgesic effect: 2 mg butorphanol, 10 mg morphine, 40 mg pentazocine and 80 mg meperidine.

After intravenous administration of butorphanol tartrate, onset and peak analgesic effect occurred by the time of first observation (30 minutes). After intramuscular administration, pain relief onset occurred at 30 minutes or less, and peak effect occurred between 30 minutes and one hour. The duration of action of Butorphanol Tartrate Injection was 3 to 4 hours when defined as the time necessary for pain intensity to return to pretreatment level or the time to retreatment.

Preanesthetic Medication

Butorphanol Tartrate Injection, (2 mg and 4 mg) and meperidine (80 mg) were studied for use as preanesthetic medication in hospitalized surgical patients. Patients received a single intramuscular dose of either butorphanol or meperidine approximately 90 minutes prior to anesthesia. The anesthesia regimen included barbiturate induction, followed by nitrous oxide and oxygen with halothane or enflurane, with or without a muscle relaxant.

Anesthetic preparation was rated as satisfactory in all 42 butorphanol injection patients regardless of the type of surgery.

Balanced Anesthesia

Butorphanol tartrate administered intravenously (mean dose 2 mg) was compared to intravenous morphine sulfate (mean dose 10 mg) as premedication shortly before thiopental induction, followed by balanced anesthesia in 50 ASA Class 1 and 2 patients. Anesthesia was then maintained by repeated intravenous doses, averaging 4.6 mg butorphanol and 22.8 mg morphine per patient.

Anesthetic induction and maintenance were generally rated as satisfactory with both butorphanol injection (25 patients) and morphine (25 patients) regardless of the type of surgery performed. Emergence from anesthesia was comparable with both agents.

Labor

[see PRECAUTIONS]

The analgesic efficacy of intravenous Butorphanol Tartrate Injection was studied in pain during labor. In a total of 145 patients butorphanol (1 mg and 2 mg) was as effective as 40 mg and 80 mg of meperidine (144 patients) in the relief of pain in labor with no effect on the duration or progress of labor. Both drugs readily crossed the placenta and entered fetal circulation. The condition of the infants in these studies, determined by Apgar scores at 1 and 5 minutes (8 or above) and time to sustained respiration, showed that butorphanol had the same effects on the infants as meperidine.

In these studies neurobehavioral testing in infants exposed to butorphanol injection at a mean of 18.6 hours after delivery, showed no significant differences between treatment groups.

Individualization of Dosage

Use of butorphanol in geriatric patients, patients with renal impairment, patients with hepatic impairment and during labor requires extra caution [see below and the appropriate sections in PRECAUTIONS].

For pain relief the recommended initial dosage regimen of Butorphanol Tartrate Injection is 1 mg IV or 2 mg IM with repeated doses every three to four hours as necessary. This dosage regimen is likely to be effective for the majority of patients. Dosage adjustments of butorphanol injection should be based on observations of its beneficial and adverse effects. The initial dose in the elderly and in patients with renal or hepatic impairment should generally be half the recommended adult dose (0.5 mg IV and 1 mg IM). Repeat doses in these patients should be determined by the patient's response rather than at fixed intervals but will generally be no less than 6 hours [see PRECAUTIONS].

The usual preoperative dose is 2 mg IM given 60 to 90 minutes before surgery or 2 mg IV shortly before induction. This is approximately equivalent in sedative effect to 10 mg morphine or 80 mg of meperidine. This single preoperative dose should be individualized based on age, body weight, physical status, underlying pathological condition, use of other drugs, type of anesthesia to be used and the surgical procedure involved.

During maintenance in balanced anesthesia the usual incremental dose of butorphanol tartrate is 0.5 to 1 mg IV. The incremental dose may be higher, up to 0.06 mg/kg (4 mg/70 kg), depending on previous sedative, analgesic, and hypnotic drugs administered. The total dose of butorphanol injection will vary; however, patients seldom require less than 4 mg or more than 12.5 mg (approximately 0.06 to 0.18 mg/kg).

As with other opioids of this class, butorphanol injection may not provide adequate intraoperative analgesia in every patient or under all conditions. A failure to achieve successful analgesia during balanced anesthesia is commonly reflected by increases in general sympathetic tone. Consequently, if blood pressure or heart rate continue to rise, consideration should be given to adding a potent volatile liquid inhalation anesthetic or another intravenous medication.

In labor, the recommended initial dose of butorphanol tartrate is 1 or 2 mg IM or IV in mothers with fetuses of 37 weeks gestation or beyond and without signs of fetal distress. Dosage adjustments of butorphanol in labor should be based on initial response with consideration given to concomitant analgesic or sedative drugs and the expected time of delivery. A dose should not be repeated in less than four hours nor administered less than four hours prior to the anticipated delivery [see PRECAUTIONS].

INDICATIONS AND USAGE

Butorphanol Tartrate Injection is indicated

- as a preoperative or pre-anesthetic medication
- as a supplement to balanced anesthesia
- for the relief of pain during labor, and
- for the management of pain severe enough to require an opioid analgesic and for which alternative treatments are inadequate.

Limitations of Use:

Because of the risks of addiction, abuse, misuse, overdose, and death, which can occur at any dosage or duration and persist over the course of therapy [see WARNINGS], reserve opioid analgesics, including butorphanol tartrate, for use in patients for whom alternative treatment options are ineffective, not tolerated, or would be otherwise inadequate to provide sufficient management of pain.

CONTRAINDICATIONS

Butorphanol Tartrate Injection is contraindicated in:

- Patients with significant respiratory depression [see WARNINGS]
- Patients with acute of severe bronchial asthma in an unmonitored setting or in the absence of resuscitative equipment [see WARNINGS]
- Patients with known or suspected gastrointestinal obstruction, including paralytic ileus [see WARNINGS]
- Patients with hypersensitivity to butorphanol tartrate or any of the formulation excipients (e.g., anaphylaxis) [see WARNINGS]

WARNINGS

Addiction, Abuse, and Misuse

Butorphanol Tartrate Injection is a Schedule IV controlled substance. As an opioid, butorphanol tartrate exposes users to the risks of addiction, abuse, and misuse [see DRUG ABUSE AND DEPENDENCE].

Although the risk of addiction in any individual is unknown, it can occur in patients appropriately prescribed butorphanol tartrate. Addiction can occur at recommended dosages and if the drug is misused or abused. The risk of opioid-related overdose or overdose-related death is increased with higher opioid doses, and this risk persists over the course of therapy. In postmarketing studies, addiction, abuse, misuse, and fatal and non-fatal opioid overdose were observed in patients with long-term opioid use [see ADVERSE REACTIONS].

Assess each patient's risk for opioid addiction, abuse, or misuse prior to prescribing Butorphanol Tartrate Injection, and monitor all patients receiving butorphanol tartrate for the development of these behaviors or conditions. Risks are increased in patients with a personal or family history of substance abuse (including drug or alcohol abuse or addiction) or mental illness (e.g., major depression). The potential for these risks should not, however, prevent the proper management of pain in any given patient. Patients at increased risk may be prescribed opioids such as Butorphanol Tartrate Injection, but use in such patients necessitates intensive counseling about the risks and proper use of Butorphanol Tartrate Injection along with frequent monitoring for signs of addiction, abuse, and misuse.

Opioids are sought for nonmedical use and are subject to diversion from ‎legitimate prescribed use. ‎Consider these risks when prescribing or dispensing Butorphanol Tartrate Injection. Strategies to reduce these risks include prescribing the drug in the smallest appropriate quantity. Contact local state professional licensing board or state-controlled substances authority for information on how to prevent and detect abuse or diversion of this product.

Life-Threatening Respiratory Depression

Serious, life-threatening, or fatal respiratory depression has been reported with the use of opioids, even when used as recommended. Respiratory depression, if not immediately recognized and treated, may lead to respiratory arrest and death. Management of respiratory depression may include close observation, supportive measures, and use of opioid overdose reversal agents (e.g., naloxone, nalmefene), depending on the patient's clinical status [see OVERDOSAGE]. Carbon dioxide (CO2) retention from opioid-induced respiratory depression can exacerbate the sedating effects of opioids.

While serious, life-threatening, or fatal respiratory depression can occur at any time during the use of butorphanol tartrate, the risk is greatest during the initiation of therapy or following a dosage increase.

To reduce the risk of respiratory depression, proper dosing and titration of butorphanol tartrate are essential [see DOSAGE AND ADMINISTRATION]. Overestimating the butorphanol tartrate dosage when converting patients from another opioid product can result in a fatal overdose with the first dose.

Opioids can cause sleep-related breathing disorders including central sleep apnea (CSA) and sleep-related hypoxemia. Opioid use increases the risk of CSA in a dose-dependent fashion. In patients who present with CSA, consider decreasing the opioid dosage using best practices for opioid taper [see DOSAGE AND ADMINISTRATION].

Risks from Concomitant Use with Benzodiazepines or Other CNS Depressants

Profound sedation, respiratory depression, coma, and death may result from the concomitant use of butorphanol tartrate with benzodiazepines and/or other CNS depressants, including alcohol (e.g., non-benzodiazepine sedatives/hypnotics, anxiolytics, tranquilizers, muscle relaxants, general anesthetics, antipsychotics, gabapentinoids [gabapentin or pregabalin], and other opioids). Because of these risks, reserve concomitant prescribing of these drugs for use in patients for whom alternative treatment options are inadequate.

Observational studies have demonstrated that concomitant use of opioid analgesics and benzodiazepines increases the risk of drug-related mortality compared to use of opioid analgesics alone. Because of similar pharmacological properties, it is reasonable to expect similar risk with the concomitant use of other CNS depressant drugs with opioid analgesics [see PRECAUTIONS; Drug Interactions].

If the decision is made to prescribe a benzodiazepine or other CNS depressant concomitantly with an opioid analgesic, prescribe the lowest effective dosages and minimum durations of concomitant use. In patients already receiving an opioid analgesic, prescribe a lower initial dose of the benzodiazepine or other CNS depressant than indicated in the absence of an opioid, and titrate based on clinical response. If an opioid analgesic is initiated in a patient already taking a benzodiazepine or other CNS depressant, prescribe a lower initial dose of the opioid analgesic, and titrate based on clinical response. Monitor patients closely for signs and symptoms of respiratory depression and sedation. Advise both patients and caregivers about the risks of respiratory depression and sedation when butorphanol tartrate is used with benzodiazepines or other CNS depressants (including alcohol and illicit drugs). Advise patients not to drive or operate heavy machinery until the effects of concomitant use of the benzodiazepine or other CNS depressant have been determined. Screen patients for risk of substance use disorders, including opioid abuse and misuse, and warn them of the risk for overdose and death associated with the use of additional CNS depressants including alcohol and illicit drugs [see PRECAUTIONS; Information for Patients, Drug Interactions].

Neonatal Opioid Withdrawal Syndrome

Use of Butorphanol Tartrate Injection for an extended period of time during pregnancy can result in withdrawal in the neonate. Neonatal opioid withdrawal syndrome, unlike opioid withdrawal syndrome in adults, may be life-threatening if not recognized and treated, and requires management according to protocols developed by neonatology experts. Advise pregnant women using opioids for an extended period of time of ‎the risk of neonatal opioid withdrawal syndrome and ensure that ‎ ‎appropriate treatment will be available [see PRECAUTIONS; Information for Patients, Pregnancy].

Opioid-Induced Hyperalgesia and Allodynia

Opioid-Induced Hyperalgesia (OIH) occurs when an opioid analgesic ‎paradoxically causes an increase in pain, or an increase in sensitivity to ‎pain. This condition differs from tolerance, which is the need for ‎increasing doses of opioids to maintain a defined effect [see Dependence]. ‎Symptoms of OIH include (but may not be limited to) increased levels of ‎pain upon opioid dosage increase, decreased levels of pain upon opioid ‎dosage decrease, or pain from ordinarily non-painful stimuli (allodynia). ‎These symptoms may suggest OIH only if there is no evidence of ‎underlying disease progression, opioid tolerance, opioid withdrawal, or addictive ‎behavior.‎

Cases of OIH have been reported, both with short-term and longer-term ‎use of opioid analgesics. Though the mechanism of OIH is not fully ‎understood, multiple biochemical pathways have been implicated. Medical ‎literature suggests a strong biologic plausibility between opioid ‎analgesics and OIH and allodynia. If a patient is suspected to be ‎experiencing OIH, carefully consider appropriately decreasing the dose of ‎the current opioid analgesic or opioid rotation (safely switching the ‎patient to a different opioid moiety) [see DOSAGE AND ADMINISTRATION; ‎WARNINGS].‎

Life-Threatening Respiratory Depression in Patients with Chronic Pulmonary Disease or in Elderly, Cachectic, or Debilitated Patients

The use of butorphanol tartrate in patients with acute or severe bronchial asthma in an unmonitored setting or in the absence of resuscitative equipment is contraindicated.

Patients with Chronic Pulmonary Disease

Butorphanol tartrate-treated patients with significant chronic obstructive pulmonary disease or cor pulmonale, and those with a substantially decreased respiratory reserve, hypoxia, hypercapnia, or pre-existing respiratory depression are at increased risk of decreased respiratory drive including apnea, even at recommended dosages of butorphanol tartrate [see WARNINGS].

Elderly, Cachectic, or Debilitated Patients

Life-threatening respiratory depression is more likely to occur in elderly, cachectic, or debilitated patients because they may have altered pharmacokinetics or altered clearance compared to younger, healthier patients [see WARNINGS].

Monitor such patients closely, particularly when initiating and titrating Butorphanol Tartrate Injection and when Butorphanol Tartrate Injection is given concomitantly with other drugs that depress respiration [see WARNINGS]. Alternatively, consider the use of non-opioid analgesics in these patients.

Adrenal Insufficiency

Cases of adrenal insufficiency have been reported with opioid use, more often following greater than 1 month of use. Presentation of adrenal insufficiency may include non-specific symptoms and signs including nausea, vomiting, anorexia, fatigue, weakness, dizziness, and low blood pressure. If adrenal insufficiency is suspected, confirm the diagnosis with diagnostic testing as soon as possible. If adrenal insufficiency is diagnosed, treat with physiologic replacement doses of corticosteroids. Wean the patient off of the opioid to allow adrenal function to recover and continue corticosteroid treatment until adrenal function recovers. Other opioids may be tried as some cases reported use of a different opioid without recurrence of adrenal insufficiency. The information available does not identify any particular opioids as being more likely to be associated with adrenal insufficiency.

Risks of Use in Patients with Increased Intracranial Pressure, Brain Tumors, Head Injury, or Impaired Consciousness

In patients who may be susceptible to the intracranial effects of CO2 retention (e.g., those with evidence of increased intracranial pressure or brain tumors), Butorphanol Tartrate Injection may reduce respiratory drive, and the resultant CO2 retention can further increase intracranial pressure. Monitor such patients for signs of sedation and respiratory depression, particularly when initiating therapy with Butorphanol Tartrate Injection.

Opioids may also obscure the clinical course in a patient with a head injury. Avoid the use of Butorphanol Tartrate Injection in patients with impaired consciousness or coma.

Risk of Gastrointestinal Complications

Butorphanol Tartrate Injection is contraindicated in patients with known or suspected gastrointestinal obstruction, including paralytic ileus.

The butorphanol in Butorphanol Tartrate Injection may cause spasm of the sphincter of Oddi. Opioids may cause increases in serum amylase. Monitor patients with biliary tract disease, including acute pancreatitis, for worsening symptoms.

Cases of opioid-induced esophageal dysfunction (OIED) have been reported in patients taking opioids. The risk of OIED may increase as the dose and/or duration of opioids increases. Regularly evaluate patients for signs and symptoms of OIED (e.g., dysphagia, regurgitation, non-cardiac chest pain) and, if necessary, adjust opioid therapy as clinically appropriate [see CLINICAL PHARMACOLOGY].

Increased Risk of Seizures in Patients with Seizure Disorders

The butorphanol in Butorphanol Tartrate Injection may increase the frequency of seizures in patients with seizure disorders, and may increase the risk of seizures occurring in other clinical settings associated with seizures. Monitor patients with a history of seizure disorders for worsened seizure control during Butorphanol Tartrate Injection therapy.

Withdrawal

The use of Butorphanol Tartrate Injection, a mixed agonist/antagonist opioid analgesic, in patients who are receiving a full opioid agonist analgesic may reduce the analgesic effect and/or precipitate withdrawal symptoms. Avoid concomitant use of Butorphanol Tartrate Injection with a full opioid agonist analgesic. When discontinuing Butorphanol Tartrate Injection, gradually taper the dosage [see DOSAGE AND ADMINISTRATION]. Do not rapidly reduce or abruptly discontinue Butorphanol Tartrate Injection [see DRUG ABUSE AND DEPENDENCE].

Cardiovascular Effects

Because butorphanol may increase the work of the heart, especially the pulmonary circuit, the use of butorphanol in patients with acute myocardial infarction, ventricular dysfunction, or coronary insufficiency should be limited to those situations where the benefits clearly outweigh the risk [see CLINICAL PHARMACOLOGY].

Severe hypertension has been reported rarely during butorphanol therapy. In such cases, butorphanol should be discontinued and the hypertension treated with antihypertensive drugs. In patients who are not opioid dependent, naloxone has also been reported to be effective.

PRECAUTIONS

General

Hypotension associated with syncope during the first hour of dosing with Butorphanol Tartrate Injection has been reported rarely, particularly in patients with past history of similar reactions to opioid analgesics. Therefore, patients should be advised to avoid activities with potential risks.

Risks of Driving and Operating Machinery

Butorphanol Tartrate Injection may impair the mental or physical abilities needed to perform potentially hazardous activities such as driving a car or operating machinery. Warn patients not to drive or operate dangerous machinery unless they are tolerant to the effects of Butorphanol Tartrate Injection and know how they will react to the medication [see PRECAUTIONS; Information for Patients/Caregivers].

Disorders of Respiratory Function or Control

Butorphanol may produce respiratory depression, especially in patients receiving other CNS active agents, or patients suffering from CNS diseases or respiratory impairment.

Hepatic and Renal Disease

In patients with hepatic or renal impairment, the initial dose of Butorphanol Tartrate Injection should generally be half the recommended adult dose (0.5 mg IV and 1 mg IM). Repeat doses in these patients should be determined by the patient's response rather than at fixed intervals but will generally be no less than 6 hours apart [see CLINICAL PHARMACOLOGY: Pharmacokinetics and Individualization of Dosage sections].

Information for Patients

Addiction, Abuse, and Misuse

Inform patients that the use of butorphanol tartrate, even when taken as recommended, can result in addiction, abuse, and misuse, which can lead to overdose and death [see WARNINGS]. Instruct patients not to share butorphanol tartrate with others and to take steps to protect butorphanol tartrate from theft or misuse.

Life-Threatening Respiratory Depression

Inform patients of the risk of life-threatening respiratory depression, including information that the risk is greatest when starting butorphanol tartrate or when the dosage is increased, and that it can occur even at recommended dosages [see WARNINGS]. Advise patients how to recognize respiratory depression and to seek medical attention if breathing difficulties develop.

Interactions with Benzodiazepines and Other CNS Depressants

Inform patients and caregivers that potentially fatal additive effects may occur if butorphanol tartrate is used with benzodiazepines or other CNS depressants, including alcohol (e.g., non-benzodiazepine sedative/hypnotics, anxiolytics, tranquilizers, muscle relaxants, general anesthetics, antipsychotics, gabapentinoids [gabapentin or pregabalin], and other opioids), and not to use these concomitantly unless supervised by a healthcare provider [see WARNINGS, PRECAUTIONS; Drug Interactions].

Hyperalgesia and Allodynia

Advise patients to seek medical attention if they ‎experience symptoms of hyperalgesia, including worsening pain, increased ‎sensitivity to pain, or new pain [see WARNINGS; ADVERSE REACTIONS].‎

Serotonin Syndrome

Inform patients that butorphanol tartrate could cause a rare but potentially life-threatening condition resulting from concomitant administration of serotonergic drugs. Warn patients of the symptoms of serotonin syndrome and to seek medical attention right away if symptoms develop after discharge from the hospital. Instruct patients to inform their healthcare providers‎ if they are taking, or plan to take serotonergic medications [see PRECAUTIONS; Drug Interactions].

Constipation

Advise patients of the potential for severe constipation, including ‎management instructions and when to seek medical attention [see ADVERSE REACTIONS].‎

Driving or Operating Heavy Machinery

Inform patients that Butorphanol Tartrate Injection may impair the mental and/or physical abilities required for the performance of potentially hazardous tasks such as driving a car or operating machinery and to avoid such tasks while taking this product, until they know how they will react to the medication.

Anaphylaxis

Inform patients that anaphylaxis has been reported with ingredients contained in Butorphanol Tartrate Injection. Advise patients how to recognize such a reaction and when to seek medical attention [see CONTRAINDICATIONS; ADVERSE REACTIONS].

Pregnancy

Neonatal Opioid Withdrawal Syndrome

Inform female patients of reproductive potential that use of Butorphanol Tartrate Injection ‎for an extended period of time during pregnancy can result in neonatal opioid withdrawal syndrome, which may be life‑threatening if not recognized and treated [see WARNINGS, PRECAUTIONS; Pregnancy].

Embryo-Fetal Toxicity

Inform female patients of reproductive potential that Butorphanol Tartrate Injection can cause fetal harm and to inform the healthcare prescriber of a known or suspected pregnancy [see PRECAUTIONS; Pregnancy].

Lactation

Advise nursing mothers to carefully observe infants for increased sleepiness (more than usual), breathing difficulties, or limpness. Instruct nursing mothers to seek immediate medical care if they notice these signs [see PRECAUTIONS; Nursing Mothers].

Infertility

Inform patients that use of opioids for an extended period of time may cause reduced fertility. It is not known whether these effects on fertility are reversible [see ADVERSE REACTIONS].

Drug Interactions

Benzodiazepines and Other Central Nervous System (CNS) Depressants

Due to additive pharmacologic effect, the concomitant use of benzodiazepines or other CNS depressants such as alcohol, sedatives/hypnotics, anxiolytics, tranquilizers, muscle relaxants, general anesthetics, antipsychotics, gabapentinoids (gabapentin or pregabalin), and other opioids, can increase the risk of respiratory depression, profound sedation, coma, and death.

Reserve concomitant prescribing of these drugs for use in patients for whom alternative treatment options are inadequate. Limit dosages and durations to the minimum required. Monitor patients closely for signs of respiratory depression and sedation [see WARNINGS]. If concomitant use is warranted, consider ‎prescribing naloxone for the emergency treatment of opioid overdose.

Serotonergic Drugs

The concomitant use of opioids with other drugs that affect the serotonergic neurotransmitter system, such as selective serotonin reuptake inhibitors (SSRIs), serotonin and norepinephrine reuptake inhibitors (SNRIs), tricyclic antidepressants (TCAs), triptans, 5-HT3 receptor antagonists, drugs that affect the serotonin neurotransmitter system (e.g., mirtazapine, trazodone, tramadol), certain muscle relaxants (eg., cyclobenzaprine, metaxalone), and monoamine oxidase (MAO) inhibitors (those intended to treat psychiatric disorders and also others, such as linezolid and intravenous methylene blue), has resulted in serotonin syndrome [see PRECAUTIONS; INFORMATION FOR PATIENTS].

If concomitant use is warranted, regularly monitor the patient, particularly during treatment initiation and dose adjustment. Discontinue Butorphanol Tartrate Injection if serotonin syndrome is suspected.

Cytochrome P450 (CYP 450) Interactions

It is not known if the effects of Butorphanol Tartrate Injection are altered by concomitant medications that affect hepatic metabolism of drugs (CYP 450 inhibitors or inducers) (e.g., erythromycin, theophylline, etc.), but physicians should be alert to the possibility that a smaller initial dose and longer intervals between doses may be needed.

Monoamine Oxidase inhibitors (MAOIs)

No information is available about the use of butorphanol concurrently with MAO inhibitors.

Advise patient to avoid concomitant use of these drugs.

Carcinogenesis, Mutagenesis, Impairment of Fertility

Carcinogenesis

Two-year carcinogenicity studies were conducted in mice and rats given butorphanol tartrate in the diet up to 60 mg/kg/day (12 and 24 times the human daily dose of 24 mg/day based on a body surface area comparison, respectively). There was no evidence of carcinogenicity in either species in these studies.

Mutagenesis

Butorphanol was not genotoxic in the in vitro bacterial reverse mutation assay (Ames) or in an in vitro unscheduled DNA synthesis and repair assay conducted in cultured human fibroblast cells.

Impairment of Fertility

In a study where male rats were treated subcutaneously with 0.5 or 2.5 mg/kg butorphanol for 75 days prior to mating to female rats treated subcutaneously with 0.5 or 2.5 mg/kg butorphanol for 14-days prior to mating and throughout gestation and lactation, no adverse effects on fertility were noted (0.2- and 1-times the human daily dose of 24 mg based on body surface area).

In a study where male rats were treated orally with 10, 40, or 160 mg/kg for 63 days prior to mating to female rats treated orally with the same doses of butorphanol for 14 days prior to mating, reduced pregnancy rates were reported in the high dose group (65-times the human daily dose of 24 mg based on body surface area).

Infertility

Use of opioids for an extended period of time may cause reduced fertility in females and males of reproductive potential.‎

Pregnancy

Reproduction studies in mice, rats, and rabbits during organogenesis did not reveal any teratogenic potential to butorphanol. However, pregnant rats treated subcutaneously with butorphanol at 1 mg/kg (5.9 mg/m^2) had a higher frequency of stillbirths than controls. Butorphanol at 30 mg/kg/oral (360 mg/m^2) and 60 mg/kg/oral (720 mg/m^2) also showed higher incidences of post‑implantation loss in rabbits.

There are no adequate and well-controlled studies of Butorphanol Tartrate Injection in pregnant women before 37 weeks of gestation. Butorphanol Tartrate Injection should be used during pregnancy only if the potential benefit justifies the potential risk to the infant.

Fetal/Neonatal Adverse Reactions

Use of opioid analgesics for an extended period of time during pregnancy for medical or nonmedical purposes can result in physical dependence in the neonate and neonatal opioid withdrawal syndrome shortly after birth.

Neonatal opioid withdrawal syndrome presents as irritability, hyperactivity and abnormal sleep pattern, high pitched cry, tremor, vomiting, diarrhea and failure to gain weight. The onset, duration, and severity of neonatal opioid withdrawal syndrome vary based on the specific opioid used, duration of use, timing and amount of last maternal use, and rate of elimination of the drug by the newborn. Observe newborns for symptoms of neonatal opioid withdrawal syndrome and manage accordingly [see WARNINGS].

Labor or Delivery

Opioids cross the placenta and may produce respiratory depression and psycho-physiologic effects in neonates. An opioid overdose reversal agent, such as naloxone or nalmefene, must be available for reversal of opioid-induced respiratory depression in the neonate. Butorphanol tartrate is not recommended for use in pregnant women during or immediately prior to labor, when other analgesic techniques are more appropriate. Opioid analgesics, including butorphanol tartrate, can prolong labor through actions which temporarily reduce the strength, duration, and frequency of uterine contractions. However, this effect is not consistent and may be offset by an increased rate of cervical dilation, which tends to shorten labor. Monitor neonates exposed to opioid analgesics during labor for signs of excess sedation and respiratory depression.

Butorphanol has been detected in milk following administration of Butorphanol Tartrate Injection to nursing mothers. The amount an infant would receive is probably clinically insignificant (estimated 4 μg/L of milk in a mother receiving 2 mg IM four times a day).

There have been rare reports of infant respiratory distress/apnea following the administration of Butorphanol Tartrate Injection during labor. The reports of respiratory distress/apnea have been associated with administration of a dose within 2 hours of delivery, use of multiple doses, use with additional analgesic or sedative drugs, or use in preterm pregnancies [see OVERDOSAGE: Treatment]. In a study of 119 patients, the administration of 1 mg of IV Butorphanol Tartrate Injection during labor was associated with transient (10–90 minutes) sinusoidal fetal heart rate patterns, but 16 was not associated with adverse neonatal outcomes. In the presence of an abnormal fetal heart rate pattern, Butorphanol Tartrate Injection should be used with caution.

Nursing Mothers

Butorphanol has been detected in milk following administration of Butorphanol Tartrate Injection to nursing mothers. The amount an infant would receive is probably clinically insignificant (estimated 4 μg/L of milk in a mother receiving 2 mg IM four times a day).

The developmental and health benefits of breastfeeding should be considered along with the mother's clinical need for butorphanol tartrate and any potential adverse effects on the breastfed infant from butorphanol tartrate or from the underlying maternal condition.

Infants exposed to butorphanol tartrate through breast milk should be monitored for excess sedation and respiratory depression. Withdrawal symptoms can occur in breastfed infants when maternal administration of an opioid analgesic is stopped, or when breast-feeding is stopped.

Pediatric Use

Butorphanol is not recommended for use in patients below 18 years of age because safety and efficacy have not been established in this population.

Geriatric Use

Elderly patients (aged 65 years or older) may have increased sensitivity to butorphanol tartrate. In general, use caution when selecting a dosage for an elderly patient, usually starting at the low end of the dosing range, reflecting the greater frequency of decreased hepatic, renal, or cardiac function and of concomitant disease or other drug therapy.

Respiratory depression is the chief risk for elderly patients treated with opioids, and has occurred after large initial doses were administered to patients who were not opioid-tolerant or when opioids were co-administered with other agents that depress respiration. Titrate the dosage of Butorphanol Tartrate Injection slowly in geriatric patients and frequently monitor the patient for signs of central nervous system and respiratory depression [see WARNINGS].

This drug is known to be substantially excreted by the kidney, and the risk of adverse reactions to this drug may be greater in patients with impaired renal function. Because elderly patients are more likely to have decreased renal function, care should be taken in dose selection, and it may be useful to monitor renal function.

ADVERSE REACTIONS

Clinical Trial Experience

A total of 1658 patients were studied in premarketing clinical trials of Butorphanol Tartrate Injection. In nearly all cases the type and incidence of side effects with butorphanol were those commonly observed with opioid analgesics.

The adverse experiences described below are based on data from short- and long-term clinical trials in patients receiving Butorphanol Tartrate Injection.

The most frequently reported adverse experiences across all clinical trials with Butorphanol Tartrate Injection and Nasal Spray were somnolence (43%), dizziness (19%), nausea and/or vomiting (13%). The following adverse experiences were reported at a frequency of 1% or greater in clinical trials and were considered to be probably related to the use of butorphanol:

Body as a Whole: Asthenia/Lethargy, Headache, Sensation of Heat

Cardiovascular: Vasodilation, Palpitations

Digestive: Anorexia, Constipation, Dry Mouth, Nausea and/or Vomiting, Stomach Pain

Nervous: Anxiety, Confusion, Dizziness, Euphoria, Floating Feeling, Insomnia, Nervousness, Paresthesia, Somnolence, Tremor

Respiratory: Cough, Dyspnea

Skin and Appendages: Sweating, Pruritus

Special Senses: Blurred Vision, Ear Pain, Tinnitus, Unpleasant Taste

The following adverse experiences were reported with a frequency of less than 1% in clinical trials and were considered to be probably related to the use of butorphanol:

Cardiovascular: Hypotension, Syncope

Nervous: Abnormal Dreams, Agitation, Dysphoria, Hallucinations, Hostility, Withdrawal Symptoms

Skin and Appendages: Rash/Hives

Urogenital: Impaired Urination

The following infrequent additional adverse experiences were reported in a frequency of less than 1% of the patients studied in short-term butorphanol tartrate nasal sprays trials and under circumstances where the association between these events and butorphanol administration is unknown. They are being listed as alerting information for the physician due to their clinical significance:

Body as a Whole: Edema

Cardiovascular: Chest Pain, Hypertension, Tachycardia

Nervous: Depression

Respiratory: Shallow Breathing

Postmarketing Experience

The following adverse reactions have been identified during post approval use of Butorphanol Tartrate Injection. Because these reactions are reported voluntarily from a population of uncertain size, it is not always possible to reliably estimate their frequency or establish a causal relationship to drug exposure.

- Serotonin syndrome: Cases of serotonin syndrome, a potentially life-threatening condition, have been reported during concomitant use of opioids with serotonergic drugs.
- Adrenal insufficiency: Cases of adrenal insufficiency have been reported with opioid use, more often following greater than one month of use.
- Anaphylaxis: Anaphylaxis has been reported with ingredients contained in Butorphanol Tartrate Injection.
- Androgen deficiency: Cases of androgen deficiency have occurred with use of opioids for an extended period of time [see CLINICAL PHARMACOLOGY].
- Hyperalgesia and Allodynia: Cases of hyperalgesia and allodynia have been ‎reported with opioid therapy of any duration [see WARNINGS].‎
- Hypoglycemia: Cases of hypoglycemia have been reported in patients ‎taking opioids. Most reports were in patients with at least one ‎predisposing risk factor (e.g., diabetes).‎
- Opioid-induced esophageal dysfunction (OIED): Cases of OIED have been reported in patients taking opioids and may occur more frequently in patients taking higher doses of opioids, and/or in patients taking opioids longer term [see WARNINGS].

Adverse Reactions from Observational Studies

A prospective, observational cohort study estimated the risks of addiction, abuse, and misuse in patients initiating long-term use of Schedule II opioid analgesics between 2017 and 2021. Study participants included in one or more analyses had been enrolled in selected insurance plans or health systems for at least one year, were free of at least one outcome at baseline, completed a minimum number of follow-up assessments, and either: 1) filled multiple extended-release/long-acting opioid analgesic prescriptions during a 90-day period (n=978); or 2) filled any Schedule II opioid analgesic prescriptions covering at least 70 of 90 days (n=1,244). Those included also had no dispensing of the qualifying opioids in the previous 6 months.

Over 12 months:

- approximately 1% to 6% of participants across the two cohorts newly met criteria for addiction, as assessed with two validated interview-based measures of moderate-to-severe opioid use disorder based on Diagnostic and Statistical Manual of Mental Disorders, Fifth Edition (DSM-5) criteria, and
- approximately 9% and 22% of participants across the two cohorts newly met criteria for prescription opioid abuse and misuse [defined in DRUG ABUSE AND DEPENDENCE], respectively, as measured with a validated self-reported instrument.

A retrospective, observational cohort study estimated the risk of opioid-involved overdose or opioid overdose-related death in patients with new long-term use of Schedule II opioid analgesics from 2006 through 2016 (n=220,249). Included patients had been enrolled in either one of two commercial insurance programs, one managed care program, or one Medicaid program for at least 9 months. New long-term use was defined as having Schedule II opioid analgesic prescriptions covering at least 70 days’ supply over the 3 months prior to study entry and none during the preceding 6 months. Patients were excluded if they had an opioid-involved overdose in the 9 months prior to study entry. Overdose was measured using a validated medical code-based algorithm with linkage to the National Death Index database. The 5-year cumulative incidence estimates for opioid-involved overdose or opioid overdose-related death ranged from approximately 1.5% to 4% across study sites, counting only the first event during follow-up. Approximately 17% of first opioid overdoses observed over the entire study period (5-11 years, depending on the study site) were fatal. Higher baseline opioid dose was the strongest and most consistent predictor of opioid-involved overdose or opioid overdose-related death. Study exclusion criteria may have selected patients at lower risk of overdose, and substantial loss to follow-up (approximately 80%) also may have biased estimates.

The risk estimates from the studies described above may not be generalizable to all patients receiving opioid analgesics, such as those with exposures shorter or longer than the duration evaluated in the studies.

DRUG ABUSE AND DEPENDENCE

Controlled Substance

Butorphanol Tartrate Injection contains butorphanol, a Schedule IV controlled substance.

Abuse

Butorphanol Tartrate Injection contains butorphanol, a substance with high potential ‎for misuse and abuse, which can lead to the development of substance use ‎disorder, including addiction [see WARNINGS].

Misuse is the intentional use, for therapeutic purposes, of a drug by an ‎individual in a way other than prescribed by a healthcare provider or for ‎whom it was not prescribed.‎

Abuse is the intentional non-therapeutic use of a drug, even once, for its desirable psychological or physiological effects.

Drug addiction is a cluster of behavioral, cognitive, and physiological phenomena that may include a strong desire to take the drug, difficulties in controlling drug use (e.g., continuing drug use despite harmful ‎consequences, giving a higher priority to drug use than other activities ‎and obligations), and possible tolerance or physical dependence.‎

Misuse and abuse of Butorphanol Tartrate Injection increases risk of overdose, which ‎may lead to central nervous system and respiratory depression, ‎hypotension, seizures, and death. The risk is increased with concurrent ‎abuse of Butorphanol Tartrate Injection with alcohol and other CNS ‎depressants. Abuse of and addiction to opioids in some individuals may ‎not be accompanied by concurrent tolerance and symptoms of physical ‎dependence. In addition, abuse of opioids can occur in the absence of ‎addiction.‎

All patients treated with opioids require careful and frequent reevaluation ‎for signs of misuse, abuse, and addiction, because use of opioid analgesic ‎products carries the risk of addiction even under appropriate medical use. ‎Patients at high risk of Butorphanol Tartrate Injection abuse include those with a history ‎of prolonged use of any opioid, including products containing butorphanol, those with a ‎history of drug or alcohol abuse, or those who use Butorphanol Tartrate Injection in ‎combination with other abused drugs.‎

“Drug-seeking” behavior is very common in persons with substance use disorders. Drug-seeking tactics include emergency calls or visits near the end of office hours, refusal to undergo appropriate examination, testing, or referral, repeated “loss” of prescriptions, tampering with prescriptions, and reluctance to provide prior medical records or contact information for other treating healthcare provider(s). “Doctor shopping” (visiting multiple prescribers to obtain additional prescriptions) is common among people who abuse drugs and people with substance use disorder. Preoccupation with achieving adequate pain relief can be appropriate behavior in a patient with inadequate pain control.

Butorphanol Tartrate Injection, like other opioids, can be diverted for nonmedical use into illicit channels of distribution. Careful record-keeping of prescribing information, including quantity, frequency, and renewal requests, as required by state and federal law, is strongly advised.

Proper assessment of the patient, proper prescribing practices, periodic reevaluation of therapy, and proper dispensing and storage are appropriate measures that help to limit abuse of opioid drugs.

Risks Specific to Abuse of Butorphanol Tartrate Injection

Abuse of Butorphanol Tartrate Injection poses a risk of overdose and death. The risk is increased with concurrent use of Butorphanol Tartrate Injection with alcohol and/or other CNS depressants.

Parenteral drug abuse is commonly associated with transmission of infectious diseases such as hepatitis and HIV.

Dependence

Both tolerance and physical dependence can develop during use of opioid therapy.

Tolerance is a physiological state characterized by a reduced response to a drug ‎after repeated administration (i.e., a higher dose of a drug is required to ‎produce the same effect ‎that was once obtained at a lower dose).‎

Physical dependence is a state that develops as a result of a physiological adaptation in ‎response to repeated drug use, manifested by withdrawal signs and ‎symptoms after abrupt discontinuation or a significant dose reduction of a ‎drug.‎

Withdrawal may be precipitated through the administration of drugs with opioid antagonist activity (e.g., naloxone, nalmefene), mixed agonist/antagonist analgesics (e.g., pentazocine, butorphanol, nalbuphine), or partial agonists (e.g., buprenorphine). Physical dependence may not occur to a clinically significant degree until after several days to weeks of continued use.

Butorphanol Tartrate Injection should not be rapidly reduced or abruptly discontinued‎ [see DOSAGE AND ADMINISTRATION]. If butorphanol tartrate is rapidly reduced or abruptly discontinued in a physically‑dependent patient, a withdrawal syndrome may occur, typically characterized by‎ restlessness, lacrimation, rhinorrhea, perspiration, chills, myalgia, and mydriasis. Other signs and symptoms also may develop, including irritability, anxiety, backache, joint pain, weakness, abdominal cramps, insomnia, nausea, anorexia, vomiting, diarrhea, or increased blood pressure, respiratory rate, or heart rate.

Infants born to mothers physical-dependent on opioids will also be physically-dependent and may exhibit respiratory difficulties and withdrawal signs [see PRECAUTIONS; Pregnancy].

OVERDOSAGE

Clinical Presentation

Acute overdose with butorphanol tartrate can be manifested by respiratory depression, somnolence progressing to stupor or coma, skeletal muscle flaccidity, cold and clammy skin, constricted pupils, and, in some cases, pulmonary edema, bradycardia, hypotension, hypoglycemia, partial or complete airway obstruction, atypical snoring, and death. Marked mydriasis rather than miosis may be seen with hypoxia in overdose situations [see CLINICAL PHARMACOLOGY]. Toxic leukoencephalopathy has been reported after opioid overdose and can present hours, days, or weeks after apparent recovery from the initial intoxication.

Treatment of Overdose

In case of overdose, priorities are the reestablishment of a patent and protected airway and institution of assisted or controlled ventilation, if needed. Employ other supportive measures (including oxygen and vasopressors) in the management of circulatory shock and pulmonary edema as indicated. Cardiac arrest or arrhythmias will require advanced life-support measures.

For clinically significant respiratory or circulatory depression secondary to butorphanol tartrate overdose, administer an opioid overdose reversal agent such as naloxone or nalmefene. As butorphanol is a mixed opioid agonist/antagonist, larger doses of naloxone or nalmefene may be needed to reverse the effects of an overdose.

Opioid antagonists should not be administered in the absence of clinically significant respiratory or circulatory depression secondary to butorphanol tartrate overdose.

Because the duration of opioid reversal is expected to be less than the duration of action of butorphanol in Butorphanol Tartrate Injection, carefully monitor the patient until spontaneous respiration is reliably re-established. If the response to an opioid overdose reversal agent is suboptimal or only brief in nature, administer additional reversal agent as directed by the product's prescribing information.

In an individual physically dependent on opioids, administration of the recommended usual dosage of the overdose reversal agent will precipitate an acute withdrawal syndrome. The severity of the withdrawal symptoms experienced will depend on the degree of physical dependence and the dose of the reversal agent administered. If a decision is made to treat serious respiratory depression in the physically-dependent patient, administration of the reversal agent should be begun with care and by titration with smaller than usual doses of the reversal agent.

DOSAGE AND ADMINISTRATION

Important Dosage and Administration Instructions

Butorphanol Tartrate Injection should be prescribed only by healthcare professionals who are ‎knowledgeable about the use of opioids and how to mitigate the ‎associated risks.‎

Use the lowest effective dosage for the shortest duration of time consistent with individual patient treatment goals [see WARNINGS]. Because the risk of overdose increases as opioid doses increase, reserve ‎titration to higher doses of Butorphanol Tartrate Injection for patients in whom lower ‎doses are insufficiently effective and in whom the expected benefits of ‎using a higher dose opioid clearly outweigh the substantial risks.‎

There is variability in the opioid analgesic dose and duration needed to ‎adequately manage pain due both to the cause of pain and to individual ‎patient factors. Initiate the dosing regimen for each patient individually, ‎taking into account the patient’s underlying cause and severity of pain, ‎prior analgesic treatment and response, and risk factors for addiction, ‎abuse, and misuse [see WARNINGS].

Respiratory depression can occur at any time during opioid therapy, ‎especially when initiating and following dosage increases with Butorphanol Tartrate Injection. Consider this risk when selecting an initial dose and when ‎making dose adjustments [see WARNINGS]‎.

Initial Dosage

Factors to be considered in determining the dose are age, body weight, physical status, underlying pathological condition, use of other drugs, type of anesthesia to be used, and surgical procedure involved. Use in the elderly, patients with hepatic or renal disease, or in labor requires extra caution [see PRECAUTIONS; CLINICAL PHARMACOLOGY: Individualization of Dosage]. The following doses are for patients who do not have impaired hepatic or renal function and who are not on CNS active agents.

Use for Pain

Intravenous

The usual recommended single-dose for IV administration is 1 mg repeated every three to four hours as necessary. The effective dosage range, depending on the severity of pain, is 0.5 to 2 mg repeated every three to four hours.

Intramuscular

The usual recommended single-dose for IM administration is 2 mg in patients who will be able to remain recumbent, in the event drowsiness or dizziness occurs. This may be repeated every three to four hours, as necessary. The effective dosage range depending on the severity of pain is 1 to 4 mg repeated every three to four hours. There are insufficient clinical data to recommend single-doses above 4 mg.

Use as Preoperative/Preanesthetic Medication

The preoperative medication dosage of Butorphanol Tartrate Injection should be individualized [see CLINICAL PHARMACOLOGY: Individualization of Dosage]. The usual adult dose is 2 mg IM, administered 60 to 90 minutes before surgery. This is approximately equivalent in sedative effect to 10 mg morphine or 80 mg meperidine.

Use in Balanced Anesthesia

The usual dose of Butorphanol Tartrate Injection is 2 mg IV shortly before induction and/or 0.5 to 1 mg IV in increments during anesthesia. The increment may be higher, up to 0.06 mg/kg (4 mg/70 kg), depending on previous sedative, analgesic, and hypnotic drugs administered. The total dose of butorphanol injection will vary; however, patients seldom require less than 4 mg or more than 12.5 mg (approximately 0.06 to 0.18 mg/kg).

Labor

In patients at full term in early labor a 1 to 2 mg dose of butorphanol tartrate IV or IM may be administered and repeated after 4 hours. Alternative analgesia should be used for pain associated with delivery or if delivery is expected to occur within 4 hours.

If concomitant use of butorphanol with drugs that may potentiate its effects is deemed necessary [see PRECAUTIONS: Drug Interactions] the lowest effective dose should be employed.

Dosage Modifications in Elderly Patients and Patients with Renal or Hepatic Impairment

The initial dose sequence in elderly patients and patients with hepatic or renal impairment should be limited to 1 mg followed, if needed, by 1 mg in 90 to 120 minutes. The repeat dose sequence should be determined by the patient's response rather than at fixed times but will generally be no less than at 6 hours intervals [see CLINICAL PHARMACOLOGY: Individualization of Dosage, PRECAUTIONS].

Titration and Maintenance of Therapy

Individually titrate Butorphanol Tartrate Injection to a dose that provides adequate analgesia and minimizes adverse reactions. Continually reevaluate patients receiving Butorphanol Tartrate Injection to assess the maintenance of pain control, signs and symptoms of opioid withdrawal, and other adverse reactions as well as reassessing for the development of addiction, abuse, or misuse [see WARNINGS]. Frequent communication is important among the prescriber, other members of the healthcare team, the patient, and the caregiver/family during periods of changing analgesic requirements, including initial titration.

If the level of pain increases after dosage stabilization, attempt to identify the source of increased pain before increasing the Butorphanol Tartrate Injection dosage. If after increasing the dosage, unacceptable opioid-related adverse reactions are observed (including an increase in pain after dosage increase), consider reducing the dosage ‎[see WARNINGS]. Adjust the dosage to obtain an appropriate balance between management of pain and opioid-related adverse reactions.

Discontinuation of Butorphanol Tartrate Injection

When a patient who has been taking Butorphanol Tartrate Injection regularly and may be physically dependent no longer requires therapy with Butorphanol Tartrate Injection, taper the dose gradually, by 25% to 50% every 2 to 4 days, while monitoring carefully for signs and symptoms of withdrawal. If the patient develops these signs or symptoms, raise the dose to the previous level and taper more slowly, either by increasing the interval between decreases, decreasing the amount of change in dose, or both. Do not rapidly reduce or abruptly discontinue Butorphanol Tartrate Injection in patients who may be physically-dependent on opioids [see WARNINGS, DRUG ABUSE AND DEPENDENCE].

Safety and Handling

Butorphanol Tartrate Injection is supplied in sealed delivery systems that have a low risk of accidental exposure to healthcare workers. Ordinary care should be taken to avoid aerosol generation while preparing a syringe for use. Following skin contact, rinsing with cool water is recommended.

The disposal of Schedule IV controlled substances must be consistent with State and Federal Regulations.

Parenteral drug products should be inspected visually for particulate matter and discoloration prior to administration, whenever solution and container permit.

HOW SUPPLIED

Butorphanol Tartrate Injection, USP is supplied as single-dose glass fliptop vials, and available as follows:

Unit of Sale | Concentration (Total Butorphanol Concentration Per Container)
NDC 0409-1623-01 Carton of 10 – 1 mL Single-Dose Glass Fliptop Vials | 1 mg/mL
NDC 0409-1626-01 Carton of 10 – 1 mL Single-Dose Glass Fliptop Vials | 2 mg/mL
NDC 0409-1626-02 Carton of 10 – 2 mL Single-Dose Glass Fliptop Vials | 4 mg/2 mL (2 mg/mL)

STORAGE AND HANDLING

Store at 20°C to 25°C (68°F to 77°F). [See USP Controlled Room Temperature.]

Protect from light.

Distributed by Hospira Inc., Lake Forest, IL 60045 USA

For Medical Information about Butorphanol Tartrate Injection, please visit ‎www.pfizermedinfo.com or call 1-800-438-1985.‎

LAB-0831-8.0

Revised: 12/2025

PRINCIPAL DISPLAY PANEL - 2 mg/mL Vial Label

1 mL
Single-dose

Rx only

BUTORPHANOL
TARTRATE Inj., USP

CIV

2 mg/mL

For I.M. or I.V. use
Dist. by Hospira, Inc., Lake Forest, IL 60045 USA

PRINCIPAL DISPLAY PANEL - 2 mg/mL Vial Carton

1 mL Single-dose Fliptop Vials
NDC 0409-1626-01
Contains 10 of NDC 0409-1626-21

BUTORPHANOL TARTRATE
Injection, USP 2 mg/mL
Rx only
CIV

For Intramuscular or Intravenous use Discard unused portion.

Hospira

PRINCIPAL DISPLAY PANEL - 4 mg/2 mL Vial Label

2 mL
Single-dose

Rx only

CIV

BUTORPHANOL
TARTRATE
Injection, USP
4 mg/2 mL (2 mg/mL)

Dist. by Hospira, Inc., Lake Forest, IL 60045 USA

PRINCIPAL DISPLAY PANEL - 4 mg/2 mL Vial Carton

2 mL Single-dose Fliptop Vials
NDC 0409-1626-02
Contains 10 of NDC 0409-1626-42

BUTORPHANOL TARTRATE
Injection, USP 4 mg/2 mL (2 mg/mL)
Rx only
CIV

For Intramuscular or Intravenous use Discard unused portion.

Hospira

PRINCIPAL DISPLAY PANEL - 1 mg/mL Vial Label

1 mL
Single-dose

Rx only

CIV

BUTORPHANOL
TARTRATE Inj., USP
1 mg/mL

For I.M. or I.V. use
Dist. by Hospira, Inc., Lake Forest, IL 60045 USA

PRINCIPAL DISPLAY PANEL - 1 mg/mL Vial Carton

1 mL Single-dose Fliptop Vials
NDC 0409-1623-01
Contains 10 of NDC 0409-1623-21

BUTORPHANOL TARTRATE
Injection, USP
1 mg/mL

For Intramuscular or Intravenous use
Discard unused portion.

CIV

Rx only

Hospira